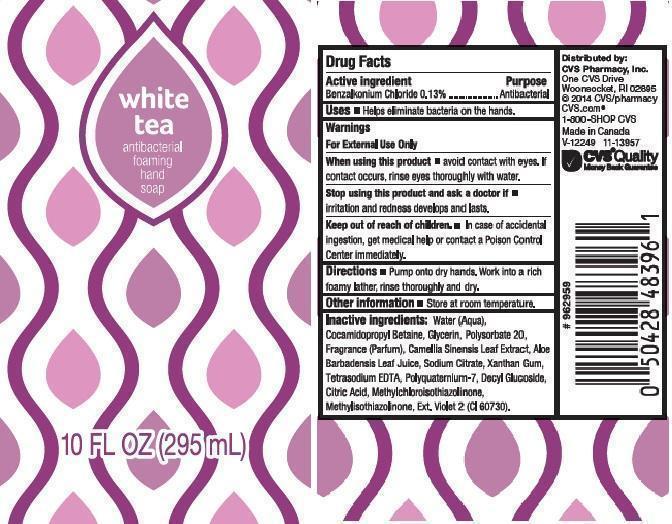 DRUG LABEL: CVS
NDC: 59779-273 | Form: LIQUID
Manufacturer: CVS PHARMACY
Category: otc | Type: HUMAN OTC DRUG LABEL
Date: 20140423

ACTIVE INGREDIENTS: BENZALKONIUM CHLORIDE 1.3 mg/1 mL
INACTIVE INGREDIENTS: WATER; COCAMIDOPROPYL BETAINE; GLYCERIN; POLYSORBATE 20; GREEN TEA LEAF; ALOE VERA LEAF; SODIUM CITRATE; XANTHAN GUM; EDETATE SODIUM; POLYQUATERNIUM-7 (70/30 ACRYLAMIDE/DADMAC; 1600000 MW); DECYL GLUCOSIDE; CITRIC ACID MONOHYDRATE; METHYLCHLOROISOTHIAZOLINONE; METHYLISOTHIAZOLINONE; EXT. D&C VIOLET NO. 2

DRUG FACTS

ACTIVE INGREDIENT

BENZALKONIUM CHLORIDE 0.13%

PURPOSE

ANTIBACTERIAL

USES

HELPS ELIMINATE BACTERIA ON THE HANDS

WARNINGS

FOR EXTERNAL USE ONLY

WHEN USING THIS PRODUCT

AVOID CONTACT WITH EYES. IF CONTACT OCCURS, RINSE EYES THOROUGHLY WITH WATER

STOP USING THIS PRODUCT AND ASK A DOCTOR IF

IRRITATION AND REDNESS DEVELOPS AND LASTS

KEEP OUT OF REACH OF CHILDREN

IN CASE OF ACCIDENTAL INGESTION, GET MEDICAL HELP OR CONTACT A POISON CONTROL CENTER IMMEDIATELY

DIRECTIONS

PUMP ONTO DRY HANDS. WORK INTO A RICH FOAMY LATHER, RINSE THOROUGHLY AND DRY

OTHER INFORMATION

STORE AT ROOM TEMPERATURE

INACTIVE INGREDIENTS

WATER (AQUA), COCAMIDOPROPYL BETAINE, GLYCERIN, POLYSORBATE 20, FRAGRANCE (PARFUM), CAMELLIA SINENSIS LEAF EXTRACT, ALOE BARBADENSIS LEAF JUICE, SODIUM CITRATE, XANTHAN GUM, TETRASODIUM EDTA, POLYQUATERNIUM-7, DECYL GLUCOSIDE, CITRIC ACID, METHYLCHLOROISOTHIAZOLINONE, METHYLISOTHIAZOLINONE, EXT. VIOLET 2 (CI 60730)